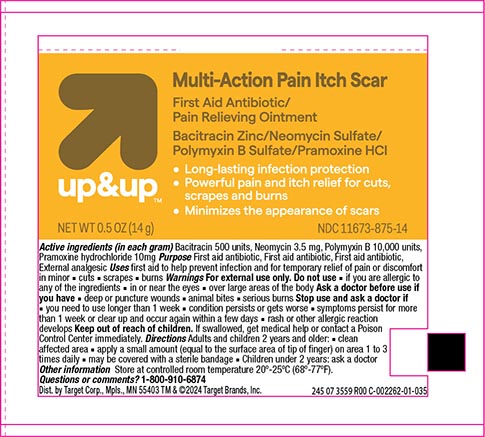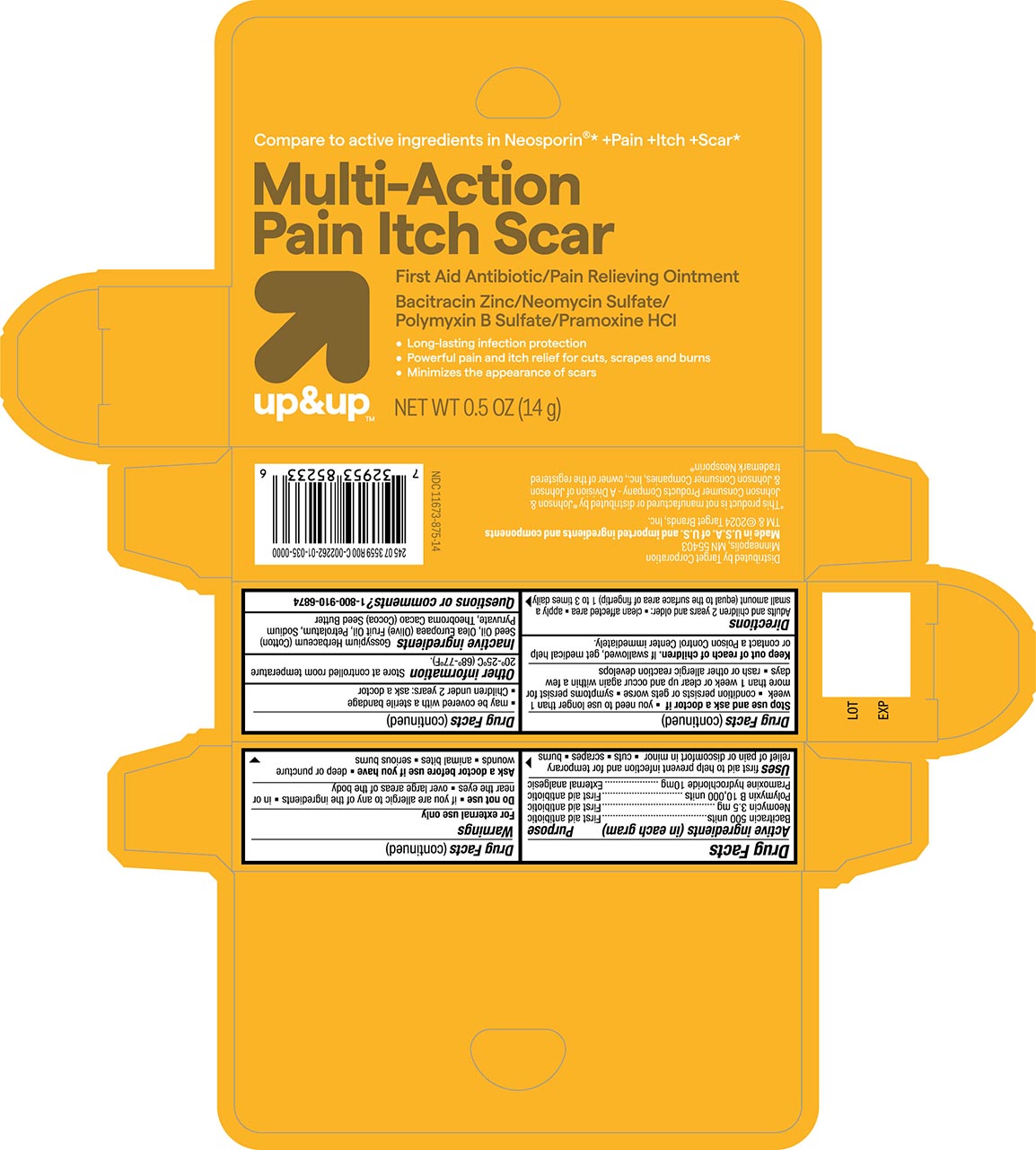 DRUG LABEL: Multi-Action Antibiotic and Pain Relief
NDC: 11673-875 | Form: OINTMENT
Manufacturer: Target Corporation
Category: otc | Type: HUMAN OTC DRUG LABEL
Date: 20240118

ACTIVE INGREDIENTS: BACITRACIN ZINC 500 [USP'U]/1 g; POLYMYXIN B SULFATE 10000 [USP'U]/1 g; NEOMYCIN SULFATE 3.5 mg/1 g; PRAMOXINE HYDROCHLORIDE 10 mg/1 g
INACTIVE INGREDIENTS: LEVANT COTTON OIL; OLIVE OIL; PETROLATUM; SODIUM PYRUVATE; COCOA BUTTER

Target Up &Up Multi-Action Antibiotic Plus Ointment

Active Ingredients

Bacitracin 500

Neomycin 3.5 mg

Polymyxin B 10,000 units

Pramoxine HCL 10 mg

Purpose

First aid antibiotic

First aid antibiotic

First aid antibiotic

Pain Relief

Uses

helps prevent infection in and temporarily relieves pain due to minor:

- cuts
- scrapes
- burns

Warnings For external use only

Do not use

- do not use if you are allergic to any of the ingredients
- or near the eyes
- or on large areas of the body

Ask a doctor before use if you have

- deep or puncture wounds
- animal bites
- serious burns

Stop use and ask a doctor if

- you need to use longer than 1 week
- condition persists or gets worse
- symptoms last for more than 7 days or clear up and come back within a few days
- a rash or other allergic reaction develops

KEEP OUT OF REACH OF CHILDREN

Keep out of the reach of children. If swallowed get medical help or contact a Poison Control Center immediately.

Directions

- clean the affected area
- apply a small amount (equal to surface area of tip of finger) on the area 1 to 3 times daily.
- may be covered with a sterile bandage

Other information

Store at a controlled room temperature 68º-77ºF (20º-25ºC)

Inactive Ingredients

Gossypium Herbaceum (Cotton) Seed Oil, Olea Europaea (Olive) Fruit Oil, Petrolatum, Sodium Pyruvate, Theobroma Cacao (Cocoa) Seed Butter, Tocopherol

Principal Display Panel

Target Up &Up NDC 11673-

Multiaction Pain Itch Scar Antibiotic ointment

Bacitracin Zinc/Neomycin Sulfate/ Polymyxin B Sulfate/ Pramoxine HCL

NET WT 0.5OZ (14g)